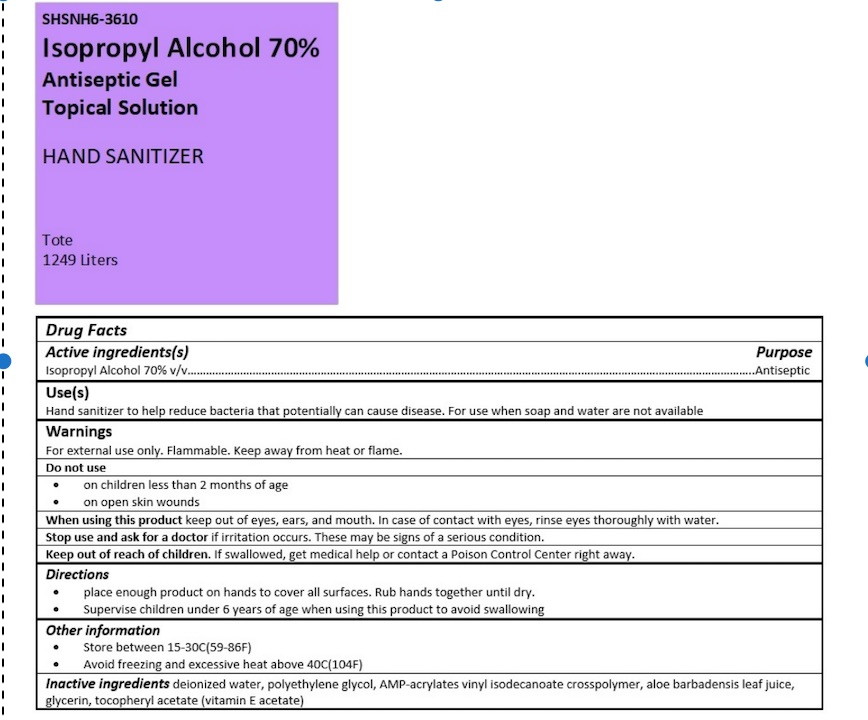 DRUG LABEL: HSUS Antiseptic Hand Sanitizer IPA
NDC: 81342-003 | Form: GEL
Manufacturer: Health Supply Us, LLC
Category: otc | Type: HUMAN OTC DRUG LABEL
Date: 20211207

ACTIVE INGREDIENTS: ISOPROPYL ALCOHOL 0.7 mL/1 mL
INACTIVE INGREDIENTS: ACRYLATES/VINYL ISODECANOATE CROSSPOLYMER (10000 MPA.S NEUTRALIZED AT 0.5%); ALOE VERA LEAF; POLYETHYLENE GLYCOL, UNSPECIFIED; AMINOMETHYLPROPANOL; WATER; ALPHA-TOCOPHEROL ACETATE; GLYCERIN

HSUS Antiseptic Hand Sanitizer IPA

Active ingredient

Isopropyl Alcohol 70%

Purpose

Antiseptic

Uses

- For hand washing to decrease bacteria on the skin
- recommended for repeated use

Warnings

For external use only

Flammable, keep away from fire or flame.

Do not use

in the eyes

Stop use and ask a doctor if

- irritation and redness develop
- condition persists for more than 72 hours

Keep out of reach of children.

If swallowed, get medical help or contact a Poison Control Center right away.

Directions

Wet hands thoroughly with product and allow to dry without wiping

Inactive ingredients

Water, Polyethylene glycol, Aminomethyl Propanol, Aloe Barbadensis Leaf Juice, Glycerin, Tocopheryl Acetate

Questions or comments?

1-888-408-1694

Package Labeling

10x10 NDC 81342-002-01